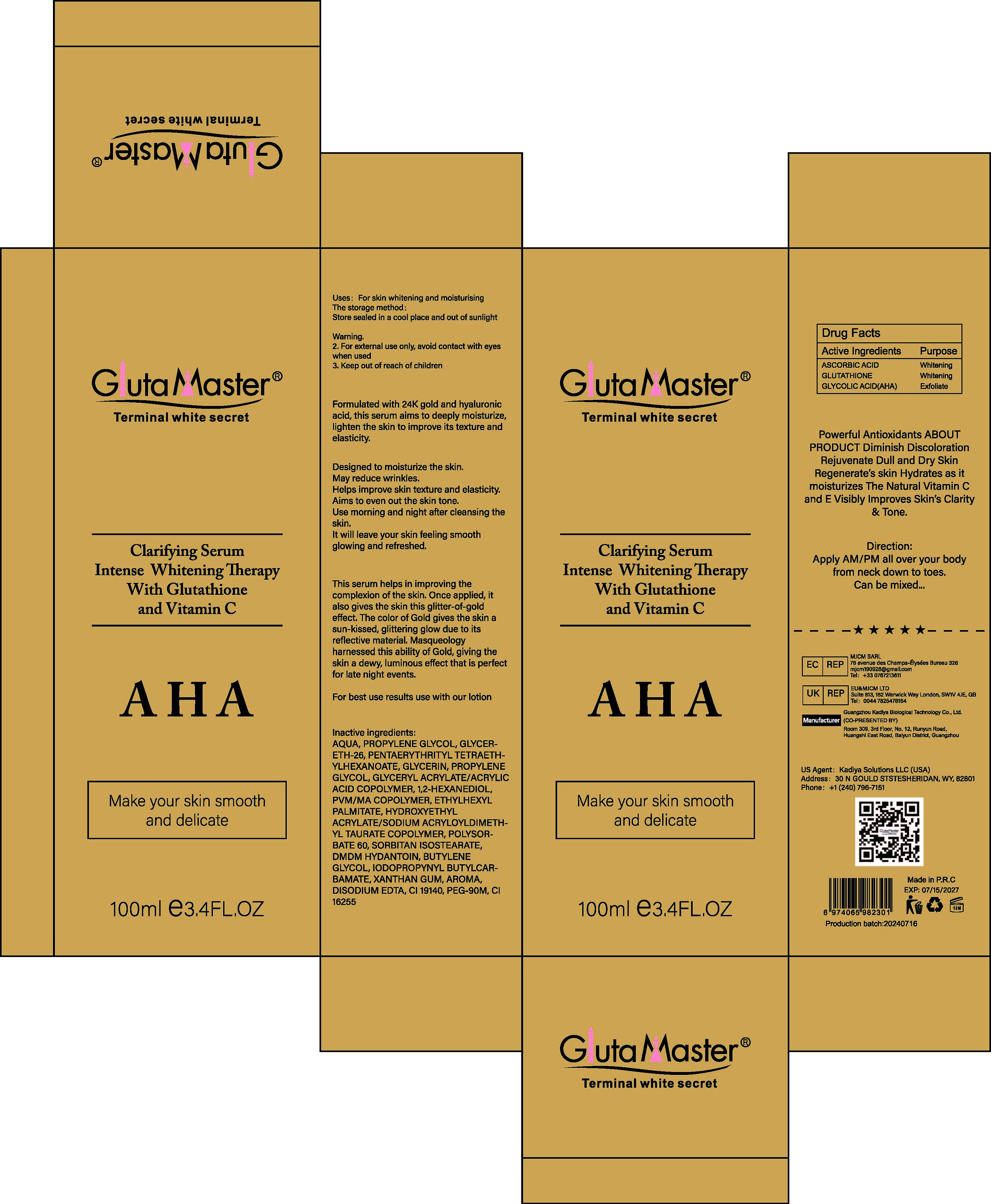 DRUG LABEL: Clarifying Serum
NDC: 84423-062 | Form: OIL
Manufacturer: Guangzhou Kadiya Biotechnology Co., Ltd.
Category: otc | Type: HUMAN OTC DRUG LABEL
Date: 20241217

ACTIVE INGREDIENTS: ASCORBIC ACID 1.3 g/100 mL; GLYCOLIC ACID 0.16 g/100 mL; GLUTATHIONE 0.49 g/100 mL
INACTIVE INGREDIENTS: GLYCERETH-26; GLYCERIN; GLYCERYL ACRYLATE/ACRYLIC ACID COPOLYMER (300000 CP AT 2%); PROPYLENE GLYCOL; PENTAERYTHRITYL TETRAETHYLHEXANOATE; SORBITAN ISOSTEARATE; IODOPROPYNYL BUTYLCARBAMATE; PEG-90M; CI 16255; POLYSORBATE 60; BUTYLENE GLYCOL; 1,2-HEXANEDIOL; CI 19140; DMDM HYDANTOIN; METHYL VINYL ETHER AND MALEIC ANHYDRIDE COPOLYMER (1100000 WAMW); XANTHAN GUM; EDETATE DISODIUM; AQUA; ETHYLHEXYL PALMITATE; HYDROXYETHYL ACRYLATE/SODIUM ACRYLOYLDIMETHYL TAURATE COPOLYMER (45000 MPA.S AT 1%)

PURPOSE

For skin whitening and moisturising

INACTIVE INGREDIENT

AQUA，PROPYLENE GLYCOL，GLYCERETH-26，PENTAERYTHRITYL TETRAETHYLHEXANOATE，GLYCERIN，PROPYLENE GLYCOL，GLYCERYL ACRYLATE/ACRYLIC ACID COPOLYMER，1,2-HEXANEDIOL，PVM/MA COPOLYMER，ETHYLHEXYL PALMITATE，HYDROXYETHYL ACRYLATE/SODIUM ACRYLOYLDIMETHYL TAURATE COPOLYMER，POLYSORBATE 60，SORBITAN ISOSTEARATE，DMDM HYDANTOIN，BUTYLENE GLYCOL，IODOPROPYNYL BUTYLCARBAMATE，XANTHAN GUM，AROMA，DISODIUM EDTA，CI 19140，PEG-90M，CI 16255

WARNINGS

1、For external use only, avoid contact with eyes when used
2、Keep out of reach of children

INDICATIONS AND USAGE

This serum helps in improving the complexion of the skin. Once applied, it also gives the skin this glitter-of-gold effect, The color of Gold gives the skin a sun-kissed, glittering glow due to its reflective material Masqueology harnessed this ability of Gold, giving the skin a dewy, luminous effect that is perfect for late night events.

DOSAGE AND ADMINISTRATION

Helps improve skin texture and elasticity.Aims to even out the skin tone.Use morning and night after cleansing the skin.

KEEP OUT OF REACH OF CHILDREN SECTION

Active Ingredients Purpose
ASCORBIC ACID Whitening
GLUTATHIONE Whitening
GLYCOLIC ACID（AHA） Exfoliate

PACKAGE LABEL

Active Ingredients Purpose
ASCORBIC ACID Whitening
GLUTATHIONE Whitening
GLYCOLIC ACID（AHA） Exfoliate

Uses：
For skin whitening and moisturising
The storage method：
Store sealed in a cool place and out of sunlight

Warning.
1、For external use only, avoid contact with eyes when used
2、Keep out of reach of children

Inactive ingredients：
AQUA，PROPYLENE GLYCOL，GLYCERETH-26，PENTAERYTHRITYL TETRAETHYLHEXANOATE，GLYCERIN，PROPYLENE GLYCOL，GLYCERYL ACRYLATE/ACRYLIC ACID COPOLYMER，1,2-HEXANEDIOL，PVM/MA COPOLYMER，ETHYLHEXYL PALMITATE，HYDROXYETHYL ACRYLATE/SODIUM ACRYLOYLDIMETHYL TAURATE COPOLYMER，POLYSORBATE 60，SORBITAN ISOSTEARATE，DMDM HYDANTOIN，BUTYLENE GLYCOL，IODOPROPYNYL BUTYLCARBAMATE，XANTHAN GUM，AROMA，DISODIUM EDTA，CI 19140，PEG-90M，CI 16255